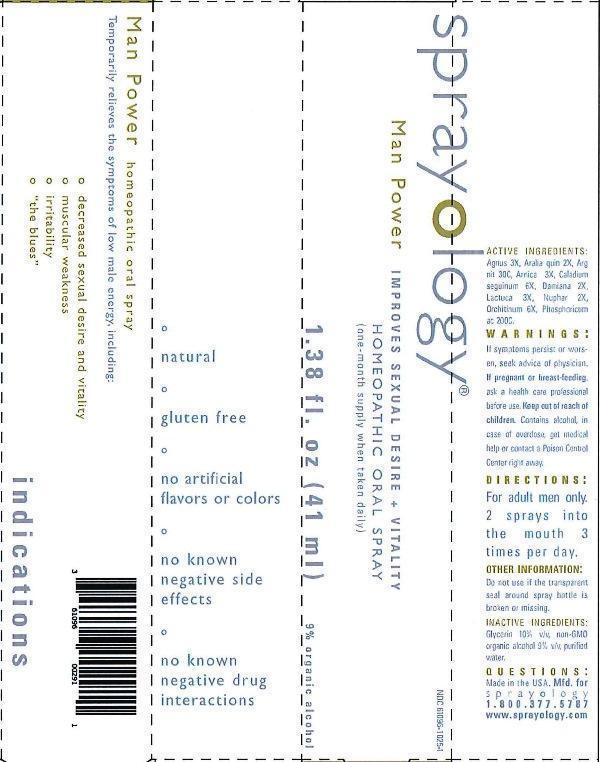 DRUG LABEL: Sprayology Man Power
NDC: 61096-1025 | Form: LIQUID
Manufacturer: Eight and Company
Category: homeopathic | Type: HUMAN OTC DRUG LABEL
Date: 20160729

ACTIVE INGREDIENTS: CHASTE TREE 3 [hp_X]/41 mL; AMERICAN GINSENG 2 [hp_X]/41 mL; SILVER NITRATE 30 [hp_C]/41 mL; ARNICA MONTANA 3 [hp_X]/41 mL; DIEFFENBACHIA SEGUINE 6 [hp_X]/41 mL; TURNERA DIFFUSA LEAFY TWIG 2 [hp_X]/41 mL; LACTUCA VIROSA 3 [hp_X]/41 mL; NUPHAR LUTEUM ROOT 2 [hp_X]/41 mL; SUS SCROFA TESTICLE 6 [hp_X]/41 mL; PHOSPHORIC ACID 200 [hp_C]/41 mL
INACTIVE INGREDIENTS: GLYCERIN; ALCOHOL; WATER

Sprayology Man Power

ACTIVE INGREDIENT

Active Ingredients: Agnus castus 3X, Aralia quinquefolia 2X, Argentum nitricum 30C, Arnica Montana 3X, Caladium seginum 6X, Damiana 2X, Lactuca virosa 3X, Nuphar Luteum 2X, Orchitinum 6X, Phosphoricum acidum 200C.

WARNINGS

Warnings: If symptoms persist or worsen, seek advice of physician. If pregnant or breast-feeding, ask a health care professional before use. Keep out of reach of children. Contains alcohol, in case of overdose, get medical help or contact a Poison Control Center right away.

Keep out of reach of children.

Directions:

- For adult men only. 2 sprays into the mouth 3 times per day.

PURPOSE

Temporarily relieves the symptoms of low male energy, including:

- decreased sexual desire and vitality
- muscular weakness
- irritability
- "the blues"

Other Information: Do not use if the transparent seal around spray bottle is broken or missing.

INACTIVE INGREDIENT

Inactive Ingredients: Glycerin 10% v/v, non-GMO organic alcohol 9% v/v and purified water.

INDICATIONS AND USAGE

Temporarily relieves the symptoms of low male energy, including:

° decreased sexual desire and vitality

° muscular weakness

° irritability

° "the blues"

° natural

° gluten free

° no artificial flavors or colors

° no known negative side effects

° no known negative drug interactions